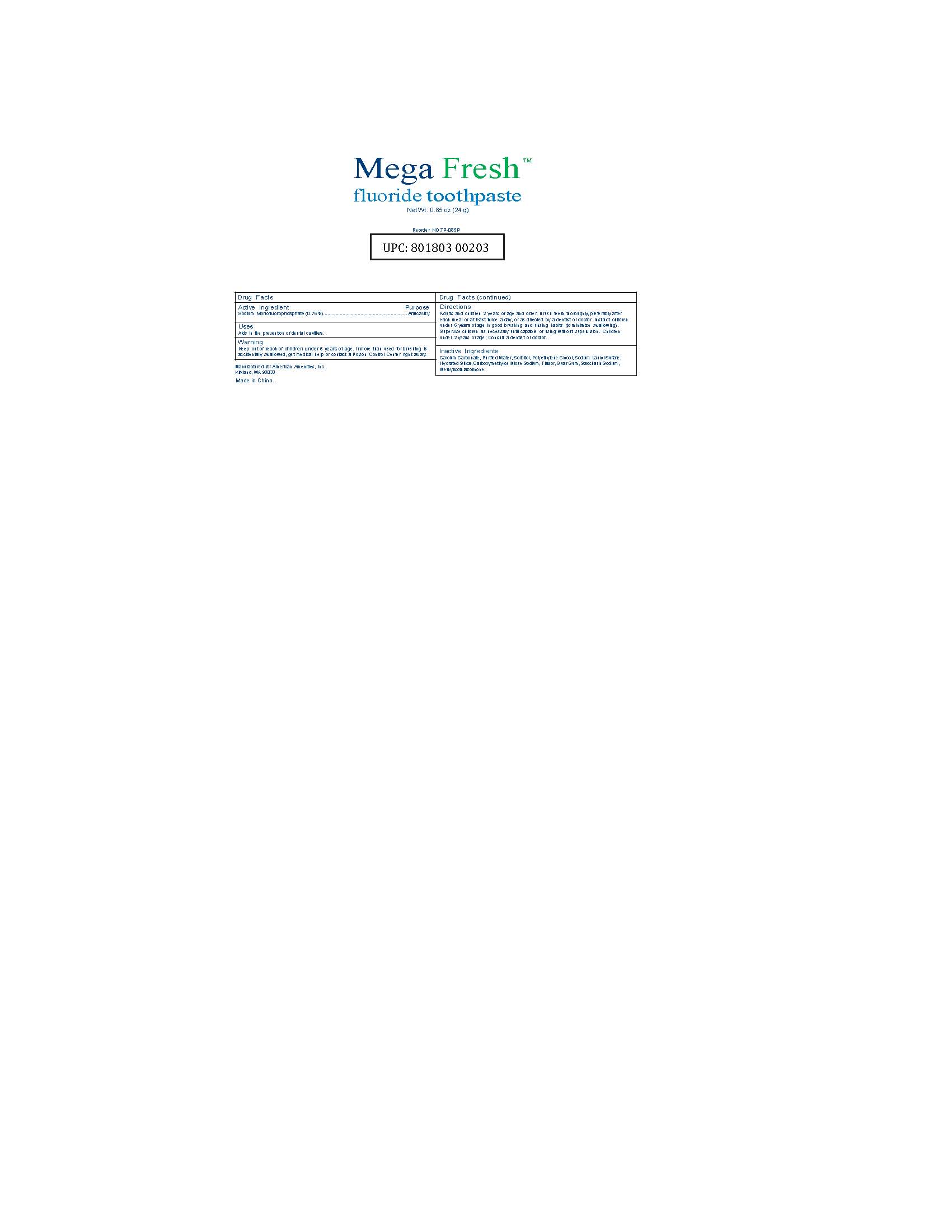 DRUG LABEL: UPC 801803 00203 MegaFresh Fluoride Tooth
NDC: 54157-108 | Form: PASTE, DENTIFRICE
Manufacturer: American Amenities, Inc.
Category: otc | Type: HUMAN OTC DRUG LABEL
Date: 20170603

ACTIVE INGREDIENTS: SODIUM MONOFLUOROPHOSPHATE 0.10 g/100 g
INACTIVE INGREDIENTS: WATER; SORBITOL; CALCIUM CARBONATE; CARBOXYMETHYLCELLULOSE SODIUM; SODIUM LAURYL SULFATE; POLYETHYLENE GLYCOL 1000; HYDRATED SILICA; SACCHARIN SODIUM; GUAR GUM; METHYLISOTHIAZOLINONE

Active Ingredient: Sodium Monofluorophosphate (0.76%)

Purpose: Anticavity

INDICATIONS AND USAGE

Uses: Aids in the prevention of dental cavities

WARNINGS

If more than used for brushing is accidentally swallowed, get medical help or contact a poison control center immediately.

Keep out of reach of children under six years of age

DOSAGE AND ADMINISTRATION

Adults and children of two years of age and older: Brush teeth thoroughly, perferrably after each meal or at least twice a day, or as directed by a dentist or a doctor. Instruct children under six years of age in good brushing and rinsing habit (to minimize swollowing). Supervise children as necessary until capable of using without supervision. Children under 2 years of age: consult a dentist or doctor.

INACTIVE INGREDIENT

Calcium Carbonate, Purified Water, Sorbitol, Polyethylene Glycol, Sodium Lauryl Sulfate, Hydrated Silica, Carboxymethylcellulose Sodium, Flavor, Guar Gum, Saccharin Sodium, Methylisothiazolinone